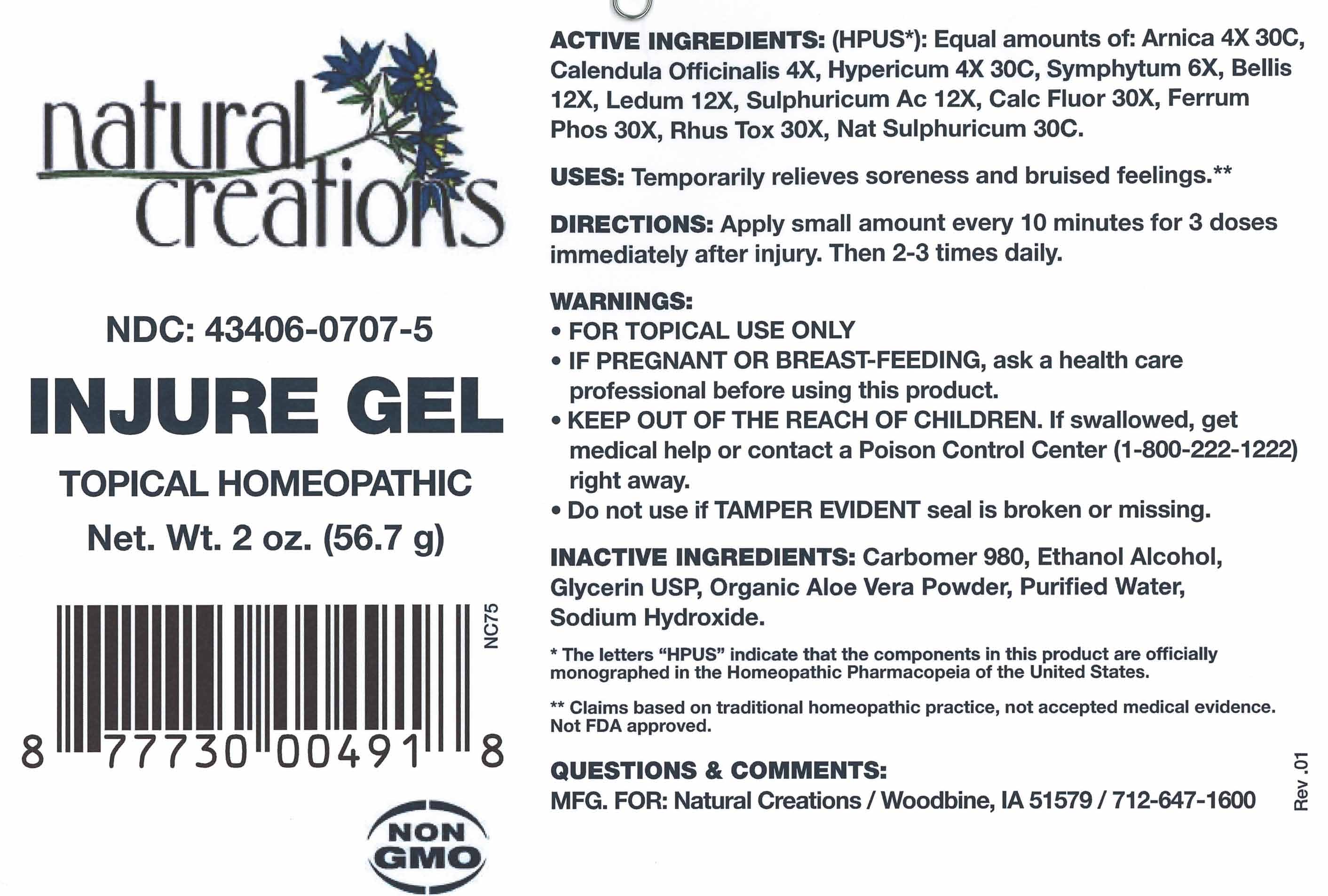 DRUG LABEL: Injure Gel
NDC: 43406-0707 | Form: GEL
Manufacturer: Natural Creations, Inc
Category: homeopathic | Type: HUMAN OTC DRUG LABEL
Date: 20181221

ACTIVE INGREDIENTS: CALENDULA OFFICINALIS FLOWERING TOP 4 [hp_X]/1 g; COMFREY ROOT 6 [hp_X]/1 g; BELLIS PERENNIS WHOLE 12 [hp_X]/1 g; RHODODENDRON TOMENTOSUM LEAFY TWIG 12 [hp_X]/1 g; SULFURIC ACID 12 [hp_X]/1 g; CALCIUM FLUORIDE 30 [hp_X]/1 g; FERROSOFERRIC PHOSPHATE 30 [hp_X]/1 g; TOXICODENDRON PUBESCENS LEAF 30 [hp_X]/1 g; ARNICA MONTANA WHOLE 30 [hp_C]/1 g; HYPERICUM PERFORATUM WHOLE 30 [hp_C]/1 g; SODIUM SULFATE 30 [hp_C]/1 g
INACTIVE INGREDIENTS: CARBOMER 980; ALCOHOL; GLYCERIN; ALOE VERA WHOLE; WATER; SODIUM HYDROXIDE

Injure Gel

ACTIVE INGREDIENT

ACTIVE INGREDIENTS (*HPUS) - equal amounts of: Arnica Montana4X, 30C, Calendula Officinalis 4X, Hypericum Perf 4X, 30C, Symphytum Off 6X, Bellis Per 12X, Ledum Palustre 12X, Sulphuricum Ac 12X, Calc Fluor 30X, Ferrum Phos 30X, Rhus Tox 30X, Nat Sulphuricum 30C

INDICATIONS AND USAGE

USES: Temporarily relieves soreness and bruised feelings.**

PURPOSE

USES: Temporarily relieves soreness and bruised feelings.**

DOSAGE AND ADMINISTRATION

DIRECTIONS: Apply small amount every 10 minutes for 3 doses immediately after injury. Then 2-3 times daily.

KEEP OUT OF REACH OF CHILDREN

KEEP OUT OF THE REACH OF CHILDREN. In case of overdose (or accidental ingestion) get medical help or contact a Poison Control Center right away.

WARNINGS:

- FOR TOPICAL USE ONLY
- Consult a physician for use in children under 12 years of age.
- IF PREGNANT OR BREAST-FEEDING, ask a health care professional before use.
- KEEP OUT OF THE REACH OF CHILDREN. In case of overdose (or accidental ingestion) get medical help or contact a Poison Control Center right away.
- Do not use if TAMPER EVIDENT seal is broken or missing.

INACTIVE INGREDIENT

INACTIVE INGREDIENTS: Carbomer 980, Ehtanol Alcohol, Glycerin USP, Organic Aloe Vera Powder, Purified Water, Sodium Hydroxide

QUESTIONS & COMMENTS?

Natural Creations, Inc. / Woodbine, IA 51579 / 712-647-1600

REFERENCES

*The letters "HPUS" indicate the components in the product are officially monographed in the Homeopathic Pharmacopeia of the United States.

**Claims based on traditional homeopathic practice, not accepted medical evidence. Not FDA evaluated.

PACKAGE LABEL

NDC:43406-0707-5

Injure Gel

HOMEOPATHIC

2 oz (56.7 g)